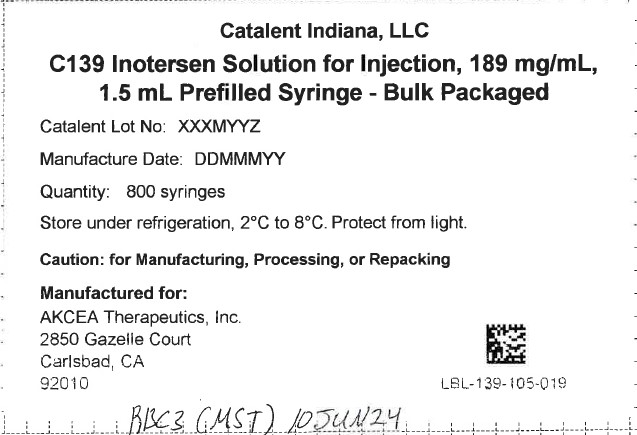 DRUG LABEL: Tegsedi
NDC: 61434-031 | Form: INJECTION, SOLUTION
Manufacturer: Catalent Indiana, LLC
Category: prescription | Type: HUMAN PRESCRIPTION DRUG LABEL
Date: 20250813

ACTIVE INGREDIENTS: INOTERSEN SODIUM 284 mg/1.5 mL

139-105-300 EXP